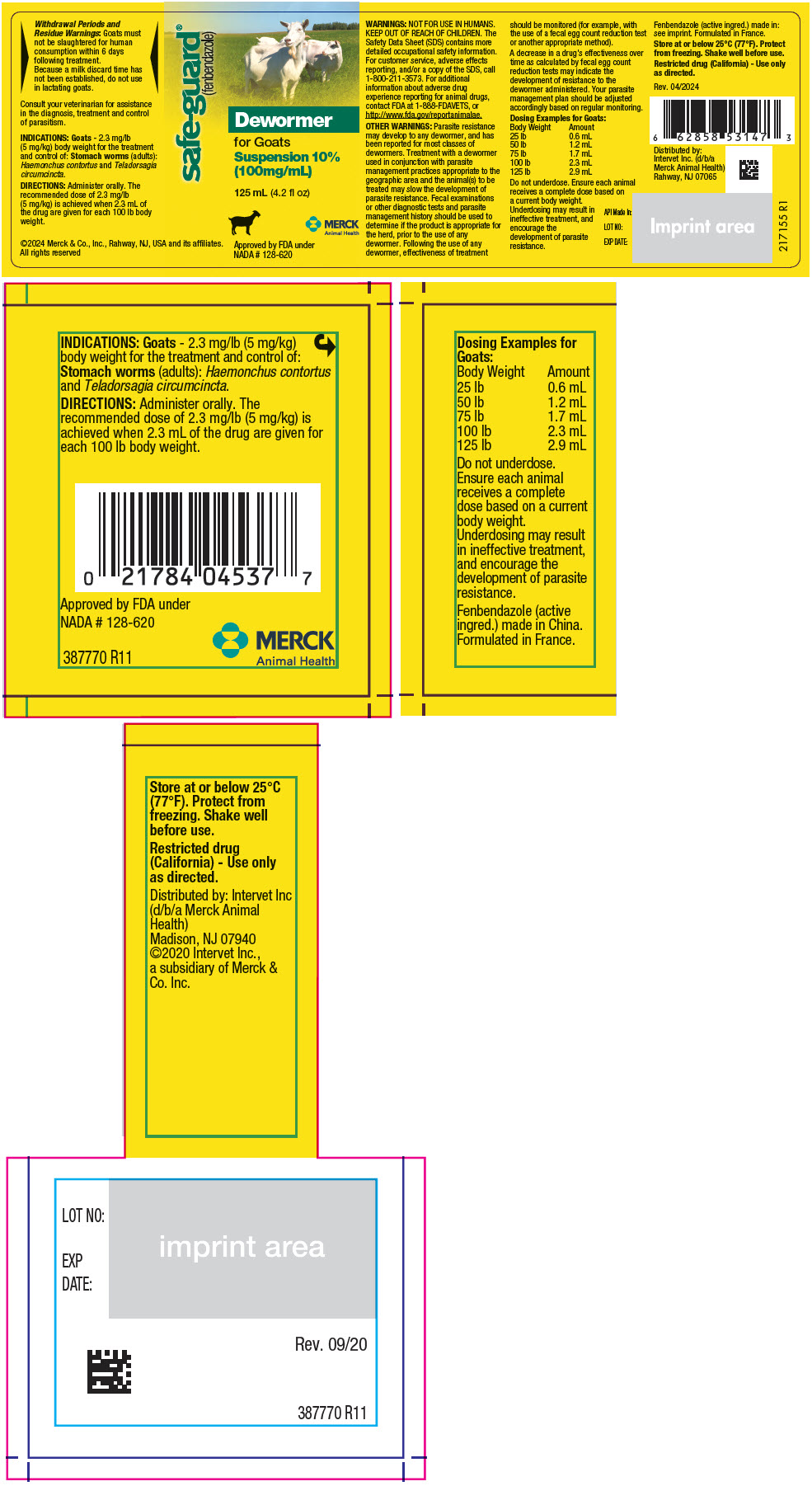 DRUG LABEL: Safe-Guard
NDC: 57926-089 | Form: SUSPENSION
Manufacturer: Merck Sharp & Dohme Corp.
Category: animal | Type: OTC ANIMAL DRUG LABEL
Date: 20241119

ACTIVE INGREDIENTS: FENBENDAZOLE 100 mg/1 mL

safe-guard®
(fenbendazole)
Dewormer

RESIDUE WARNING

Withdrawal Periods and Residue Warnings: Goats must not be slaughtered for human consumption within 6 days following treatment.

Because a milk discard time has not been established, do not use in lactating goats.

Consult your veterinarian for assistance in the diagnosis, treatment and control of parasitism.

VETERINARY INDICATIONS

INDICATIONS: Goats - 2.3 mg/lb (5 mg/kg) body weight for the treatment and control of: Stomach worms (adults): Haemonchus contortus and Teladorsagia circumcincta.

DOSAGE AND ADMINISTRATION

DIRECTIONS: Administer orally. The recommended dose of 2.3 mg/lb (5 mg/kg) is achieved when 2.3 mL of the drug are given for each 100 lb body weight.

WARNINGS

WARNINGS: NOT FOR USE IN HUMANS. KEEP OUT OF REACH OF CHILDREN. The Safety Data Sheet (SDS) contains more detailed occupational safety information. For customer service, adverse effects reporting, and/or a copy of the SDS, call 1-800-211-3573. For additional information about adverse drug experience reporting for animal drugs, contact FDA at 1-888-FDAVETS, or http://www.fda.gov/reportanimalae.

OTHER WARNINGS: Parasite resistance may develop to any dewormer, and has been reported for most classes of dewormers. Treatment with a dewormer used in conjunction with parasite management practices appropriate to the geographic area and the animal(s) to be treated may slow the development of parasite resistance. Fecal examinations or other diagnostic tests and parasite management history should be used to determine if the product is appropriate for the herd, prior to the use of any dewormer. Following the use of any dewormer, effectiveness of treatment should be monitored (for example, with the use of a fecal egg count reduction test or another appropriate method).

A decrease in a drug's effectiveness over time as calculated by fecal egg count reduction tests may indicate the development of resistance to the dewormer administered. Your parasite management plan should be adjusted accordingly based on regular monitoring.

DOSAGE AND ADMINISTRATION

Dosing Examples for Goats:

Body Weight | Amount
25 lb | 0.6 mL
50 lb | 1.2 mL
75 lb | 1.7 mL
100 lb | 2.3 mL
125 lb | 2.9 mL

Do not underdose. Ensure each animal receives a complete dose based on a current body weight.

Underdosing may result in ineffective treatment, and encourage the development of parasite resistance.

Fenbendazole (active ingred.) made in: see imprint. Formulated in France.

STORAGE AND HANDLING

Store at or below 25°C (77°F). Protect from freezing. Shake well before use.

Restricted drug (California) - Use only as directed.

Rev. 04/2024

Distributed by:
Intervet Inc. (d/b/a
Merck Animal Health)
Rahway, NJ 07065

©2024 Merck & Co., Inc., Rahway, NJ, USA and its affiliates.
All rights reserved

Approved by FDA under NADA # 128-620

217155 R1

PRINCIPAL DISPLAY PANEL - 125 mL Bottle Label

safe-guard®
(fenbendazole)

Dewormer
for Goats

Suspension 10%
(100mg/mL)

125 mL (4.2 fl oz)

MERCK
Animal Health